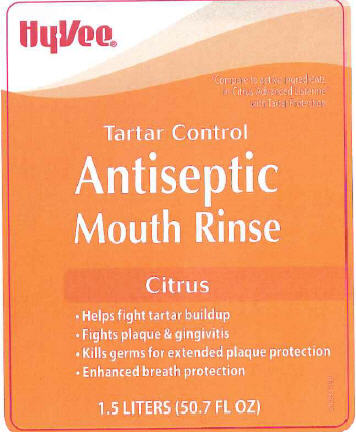 DRUG LABEL: Antiseptic Mouth Rinse
NDC: 42507-210 | Form: MOUTHWASH
Manufacturer: Hy-Vee, Inc
Category: otc | Type: HUMAN OTC DRUG LABEL
Date: 20250220

ACTIVE INGREDIENTS: EUCALYPTOL 0.092 mg/1 mL; MENTHOL 0.042 mg/1 mL; METHYL SALICYLATE 0.06 mg/1 mL; THYMOL 0.064 mg/1 mL
INACTIVE INGREDIENTS: WATER; ALCOHOL; SORBITOL; POLYOXYL 40 HYDROGENATED CASTOR OIL; POLOXAMER 407; BENZOIC ACID; ZINC CHLORIDE; SUCRALOSE; SODIUM BENZOATE; FD&C YELLOW NO. 6; FD&C RED NO. 40

Hy-Vee 210
Citrus Tartar Control

ACTIVE INGREDIENTS

Eucalyptol 0.092%

Menthol 0.042%

Methyl sailcylate 0.060%

THYMOL 0.064%

Purpose

Antigingivitis

Use

helps control plaque that leads to gingivitis

Warnings

for this product

Do not use

if you have painful or swollen gums, pus from the gum line, loose teeth or increased spacing between the teeth. See your dentist immediately. These may be signs of periodontitis, a serious form of gum disease

Stop use and ask a dentist if

gingivitis, bleeding, or redness persists for more than 2 weeks

Keep out of reach of children.

If more than used for rinsing is accidentally swallowed, get medical help or contact a Poison Control Center right away

Directions

adults and children 12 years
of age and older - vigorously swish20 mL (2/3 FL OZ or 4 teaspoonfuls) between teeth for 30 seconds then spit out; do not swallow

children under 12 years of age - consult a dentist or doctor

• this rinse is not intended to replace brushing or flossing

Other information

cold weather may cloud this product. Its antiseptic properties are not affected. Store at room temperature (59⁰- 77⁰F)

Inactive ingredients

water, alcohol (21.6%), sorbitol solution, flavoring, PEG-40 hydrogenated castor oil, poloxamer 407, benzoic acid, zinc chloride, sucralose and/or sodium saccharin, sodium benzoate, yellow 6, red 40

Disclaimer

This product is not manufactured or distributed by Johnson + Johnson Healthcare Products, distributor of Listerine

ADVERSE REACTION

DISTRIBUTED BY HY-VEE, INC

5820 WESTOWN PARKWAY

WEST DES MOINES, IA 50266

SATISFACTION GUARANTEED

OR PURCHASE PRICE REFUNDED

FOR INFORMATON CALL

1-800-289-8343

www.hy-vee.com

claims

DSP-TN-15000

DSP-MO-34

SDS-TN-15012

PRINCIPAL DISPLAY PANEL

Compare to active ingredients
in Citrus Advanced Listerine
with Tartar Protection
Tartar Control
Antiseptic
Mouth Rinse
Citrus
•Helps fight tartar buildup
•Fights plaque + gingivitis
•Kills germs for extended plaque protection
•Enhanced breath protection
1.5 LITERS (50.7 FL OZ)